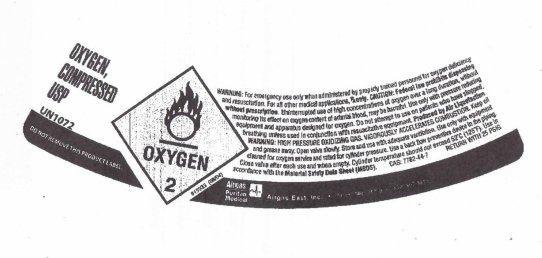 DRUG LABEL: Compressed Oxygen
NDC: 25543-200 | Form: GAS
Manufacturer: Airgas, Inc.
Category: prescription | Type: HUMAN PRESCRIPTION DRUG LABEL
Date: 20220216

ACTIVE INGREDIENTS: OXYGEN 1 L/1 L

Tri-Med Medical Compressed Oxygen

PACKAGE LABEL

OXYGEN, COMPRESSED USP
UN1072

DO NOT REMOVE THIS PRODUCT LABEL

WARNING: For emergency use only when administered by properly trained personnel for oxygen deficiency
and resuscitation. For all other medical applications, Rx only. CAUTION: Federal law prohibits dispensing
without prescription. Uninterrupted use of high concentrations of oxygen over a long duration, without
monitoring its effect on oxygen content of arterial blood, may be harmful. Use only with pressure reducing
equipment and apparatus designed for oxygen. Do not attempt to use on patients who have stopped
breathing unless used in conjunction with resuscitation equipment. Produced by Air Liquefaction.
WARNING: HIGH PRESSURE OXIDIZING GAS VIGOROUSLY ACCELERATES COMBUSTION. Keep oil
and grease away. Open valve slowly. Store and use with adequate ventilation. Use only with equipment
cleaned for oxygen service and rated for cylinder pressure. Use a back flow prevention device in the piping.
Close valve after each use and when empty. Cylinder temperature should not exceed 52C (125F). Use in
accordance with the Material Safety Data Sheet (MSDS).
CAS: 7782-44-7 RETURN WITH 25 PSIG